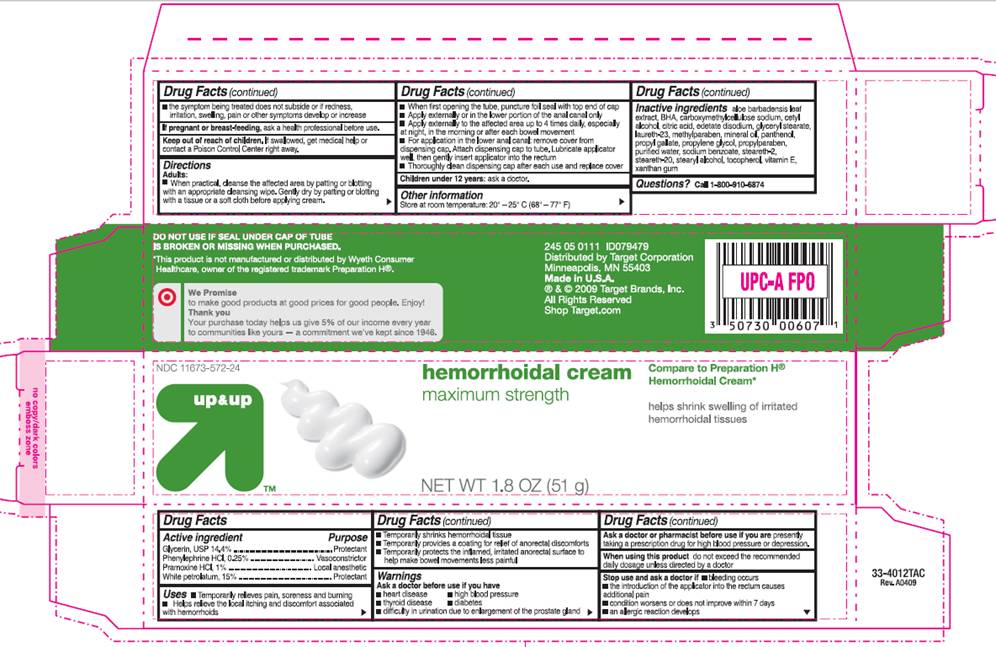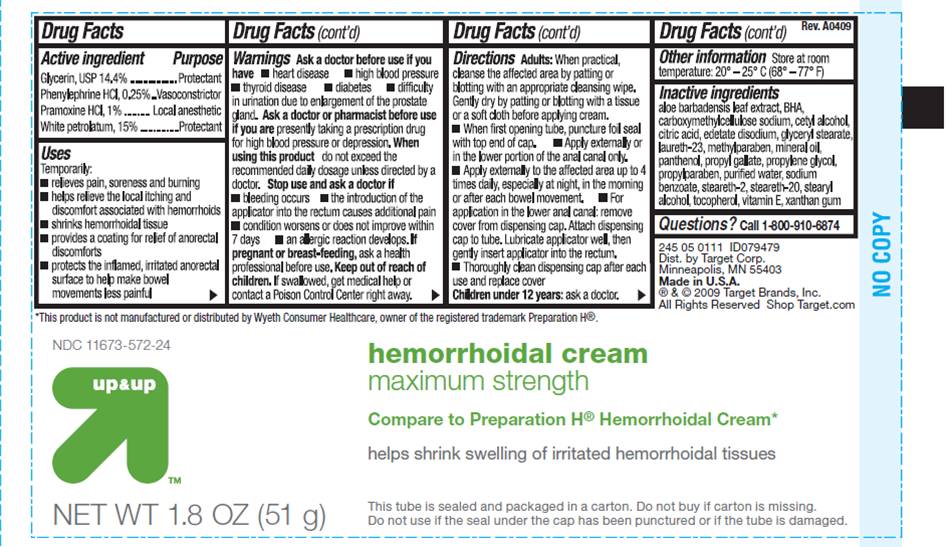 DRUG LABEL: glycerin, phenylephrine hydrochloride, pramoxine, white petrolatum
NDC: 11673-572 | Form: CREAM
Manufacturer: Target Corporation
Category: otc | Type: HUMAN OTC DRUG LABEL
Date: 20100201

ACTIVE INGREDIENTS: GLYCERIN 0.144 mg/1 g; PHENYLEPHRINE HYDROCHLORIDE 0.0025 mg/1 g; PRAMOXINE HYDROCHLORIDE 0.01 mg/1 g; PETROLATUM 0.15 mg/1 g
INACTIVE INGREDIENTS: ALOE VERA LEAF; BUTYLATED HYDROXYANISOLE; CARBOXYMETHYLCELLULOSE SODIUM; CETYL ALCOHOL; ANHYDROUS CITRIC ACID; EDETATE DISODIUM; GLYCERYL MONOSTEARATE; LAURETH-23; METHYLPARABEN; LIGHT MINERAL OIL; PANTHENOL; PROPYL GALLATE; PROPYLENE GLYCOL; PROPYLPARABEN; WATER; SODIUM BENZOATE; STEARYL ALCOHOL; ALPHA-TOCOPHEROL; .ALPHA.-TOCOPHEROL ACETATE, DL-; XANTHAN GUM

DRUG FACTS

ACTIVE INGREDIENTS

Glycerin, USP 14.4%
Phenylephrine HCI, 0.25%
Pramoxine HCI, 1%
White petrolatum, 15%

PURPOSE

Protectant

Vasoconstrictor

Local anesthetic

Protectant

USES

- Temporarily relieves pain, soreness and burning
- Helps relieve the local itching and discomfort associated with hemorrhoids
- Temporarily shrinks hemorrhoidal tissue
- Temporarily provides a coating for relief of anorectal discomforts
- Temporarily protects the inflamed, irritated anorectal surface to help make bowel movements less painful

WARNINGS

Ask a doctor before use if you have

- heart disease
- thyroid disease
- high blood pressure
- diabetes
- difficulty in urination due to enlargement of the prostate gland

Ask a doctor or pharmacist before use if you are

presently taking a prescription drug for high blood pressure or depression.

When using this product

do not exceed the recommended daily dosage unless directed by a doctor

Stop use and ask a doctor if

- bleeding occurs
- the introduction of the applicator causes additional pain
- condition worsens or does not improve within 7 days
- an allergic reaction develops
- the symptom being treated does not subside or if redness, irritation, swelling, pain or other symptoms develop or increase

If pregnant or breastfeeding

ask a health professional before use.

Keep out of reach of children

If swallowed, get medical help or contact a Poison Control Center right away.

DIRECTIONS

Adults:

- When practical, cleanse the affected area by patting or blotting with an appropriate cleansing wipe. Gently dry by patting or blotting with a tissue or soft cloth before applying cream.
- When first opening the tube, puncture foil seal with top end of cap
- Apply externally or in the lower portion of the anal canal only
- Apply externally to the affected area up to 4 times daily, especially at night, in the morning or after each bowel movement
- For application in the lower anal canal: remove cover from dispensing cap. Attach dispensing cap to tube. Lubricate applicator well, then gently insert applicator into the rectum.
- Thoroughly clean dispensing cap after each use and replace cover

Children under 12 years: ask a doctor.

OTHER INFORMATION

Store at room temperature: 20° - 25° C (68° - 77° F)

INACTIVE INGREDIENTS

aloe barbadensis leaf extract, BHA, carboxymethylcellulose sodium, cetyl alcohol, citric acid, edetate disodium, glyceryl stearate, laureth-23, methylparaben, mineral oil, panthenol, propyl gallate, propylene glycol, propylparaben, purified water, sodium benzoate, steareth-2, steareth-20, stearyl alcohol, tocopherol. vitamin E, xanthan gum

Questions?

Call 1-800-910-6874

PACKAGE INFORMATION - TUBE

up and up
NDC 11673-572-24
Hemorrhoidal Cream
maximum strength
Compare to Preparation H® Hemorrhoidal Cream*
Helps shrink swelling of irritated hemorrhoidal tissues
NET WT 1.8 OZ (51 g)
This tube is sealed and packaged in a carton. Do not buy if carton is missing . Do not use if the seal under the cap has been punctured or if the tube is damaged.
*This product is not manufactured or distributed by Wyeth Consumer Healthcare, owner of the registered trademark Preparation H®.
Dist. by Target Corp.
Minneapolis, MN 55403
Made in U.S.A.
® and © 2009 Target Brands, Inc.
All Rights Reserved
Shop Target.com

PACKAGE INFORMATION - BOX

up and up
NDC 11673-572-24
Hemorrhoidal Cream
maximum strength
Compare to Preparation H® Hemorrhoidal Cream*
Helps shrink swelling of irritated hemorrhoidal tissues
NET WT 1.8 OZ (51 g)
DO NOT USE IF SEAL UNDER CAP OF TUBE IS BROKEN OR MISSING WHEN PURCHASED.
*This product is not manufactured or distributed by Wyeth Consumer Healthcare, owner of the registered trademark Preparation H®.
Distributed by Target Corporation
Minneapolis, MN 55403
Made in U.S.A.
® and © 2009 Target Brands, Inc.
All Rights Reserved
Shop Target.com